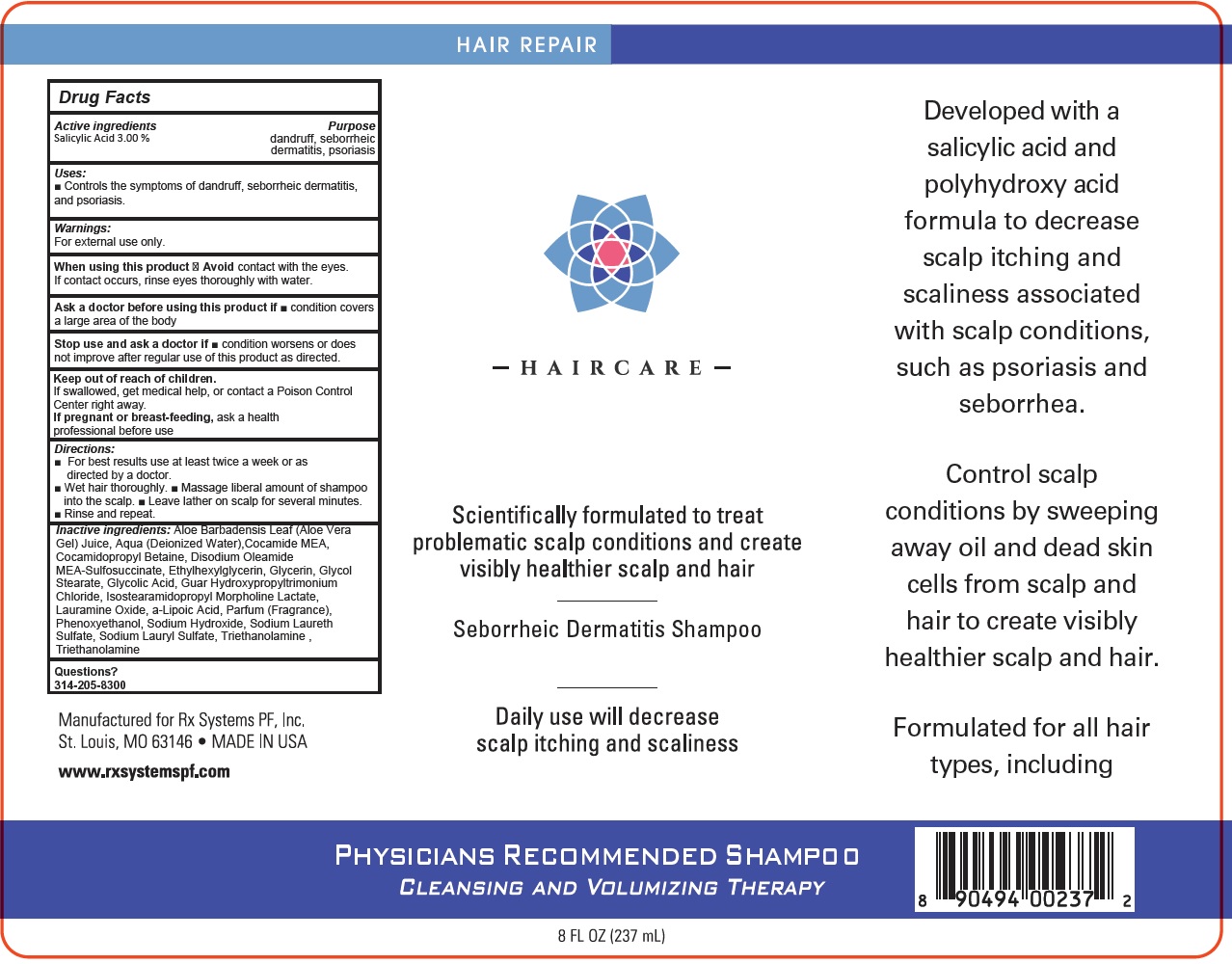 DRUG LABEL: HAIRCARE Physicians Recommended
NDC: 82499-267 | Form: SHAMPOO
Manufacturer: LAWRENCE E SAMUELS MD INC
Category: otc | Type: HUMAN OTC DRUG LABEL
Date: 20231111

ACTIVE INGREDIENTS: SALICYLIC ACID 30 mg/1 mL
INACTIVE INGREDIENTS: ALOE VERA LEAF; WATER; COCO MONOETHANOLAMIDE; COCAMIDOPROPYL BETAINE; DISODIUM OLEAMIDO MONOETHANOLAMINE SULFOSUCCINATE; ETHYLHEXYLGLYCERIN; GLYCERIN; GLYCOL STEARATE; GLYCOLIC ACID; GUAR HYDROXYPROPYLTRIMONIUM CHLORIDE (1.7 SUBSTITUENTS PER SACCHARIDE); ISOSTEARAMIDOPROPYL MORPHOLINE LACTATE; LAURAMINE OXIDE; PHENOXYETHANOL; SODIUM HYDROXIDE; SODIUM LAURETH SULFATE; SODIUM LAURYL SULFATE; TROLAMINE

HAIRCARE Physician's Recommended Shampoo

Active ingredients

Salicylic Acid 3.00 %

Purpose

dandruff, seborrheic

dermatitis, psoriasis

Uses:

- Controls the symptoms of dandruff, seborrheic dermatitis, and psoriasis.

Warnings:

For external use only.

When using this product

contact with the eyes. If contact occurs, rinse eyes thoroughly with water. Avoid

Ask a doctor before using this product if

- condition covers a large area of the body

Stop use and ask a doctor if

- condition worsens or does not improve after regular use of this product as directed.

Keep out of reach of children.

If swallowed, get medical help, or contact a Poison Control Center right away.

If pregnant or breast-feeding,

ask a health professional before use

Directions:

- For best results use at least twice a week or as directed by a doctor.
- Wet hair thoroughly.
- Massage liberal amount of shampoo into the scalp.
- Leave lather on scalp for several minutes.
- Rinse and repeat.

Inactive ingredients:

Aloe Barbadensis Leaf (Aloe Vera Gel) Juice, Aqua (Deionized Water),Cocamide MEA, Cocamidopropyl Betaine, Disodium Oleamide MEA-Sulfosuccinate, Ethylhexylglycerin, Glycerin, Glycol Stearate, Glycolic Acid, Guar Hydroxypropyltrimonium Chloride, Isostearamidopropyl Morpholine Lactate, Lauramine Oxide, a-Lipoic Acid, Parfum (Fragrance), Phenoxyethanol, Sodium Hydroxide, Sodium Laureth Sulfate, Sodium Lauryl Sulfate, Triethanolamine

Questions?

314-205-8300